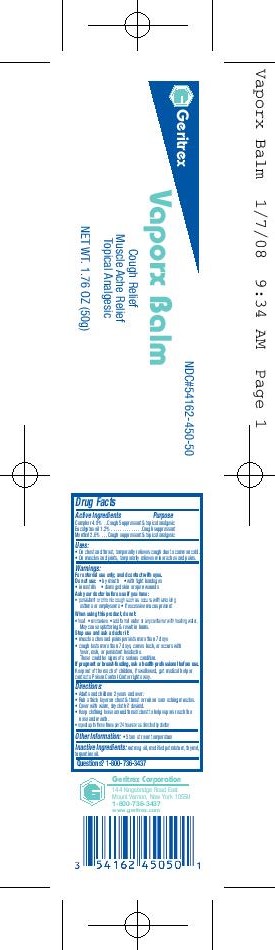 DRUG LABEL: Vaporx Balm
NDC: 54162-450 | Form: OINTMENT
Manufacturer: Geritrex LLC
Category: otc | Type: HUMAN OTC DRUG LABEL
Date: 20151230

ACTIVE INGREDIENTS: CAMPHOR (SYNTHETIC) 2.4 g/50 g; EUCALYPTUS OIL 0.6 g/50 g; MENTHOL 1.3 g/50 g
INACTIVE INGREDIENTS: NUTMEG OIL; PETROLATUM; THYMOL; TURPENTINE OIL

Vaporx Balm

Active Ingredients:

Camphor 4.8%
Eucalyptus Oil 1.2%
Menthol 2.6%

Purpose:

Camphor - Cough Suppressant and Topical Analgesic
Eucalyptus Oil- Cough Suppressant
Menthol- Cough Suppressant and Topical Analgesic

Uses:

- On chest and throat, temporarily relieves cough due to common cold

- On muscles and joints, temporarily relieves minor aches and pains

Warnings:

For external use only; avoid contact with eyes

Do not use: - by mouth - with tight bandages
- in nostrils - damaged skin or open wounds

Ask your doctor before use if you have:

- Persistent or chronic cough such as occurs with smoking, asthma or emphysema. - If excessive mucous present

When using this product, do not:

- heat - microwave - add to hot water or any container with heating water.
May cause splattering and result in burns

Stop use and ask doctor if:

- muscle aches and pains persists more than 7 days
- cough lasts more than 7 days, comes back, or occurs with fever, rash, or persistent headache.
These could be signs of a serious condition

Directions:

- Adults and children 2 years and over
- Rub a thick layer on chest & throat or rub on sore aching muscles
- Cover with warm, dry cloth if desired.
- Keep clothing loose around throat/chest to help vapors reach the nose and mouth
- repeat up to three times per 24 hours or as directed by doctor

Other Information: Store at room temperature

Inactive Ingredients:

nutmeg oil, modified petrolatum, thymol, turpentine oil

Questions? 1-800-736-3437